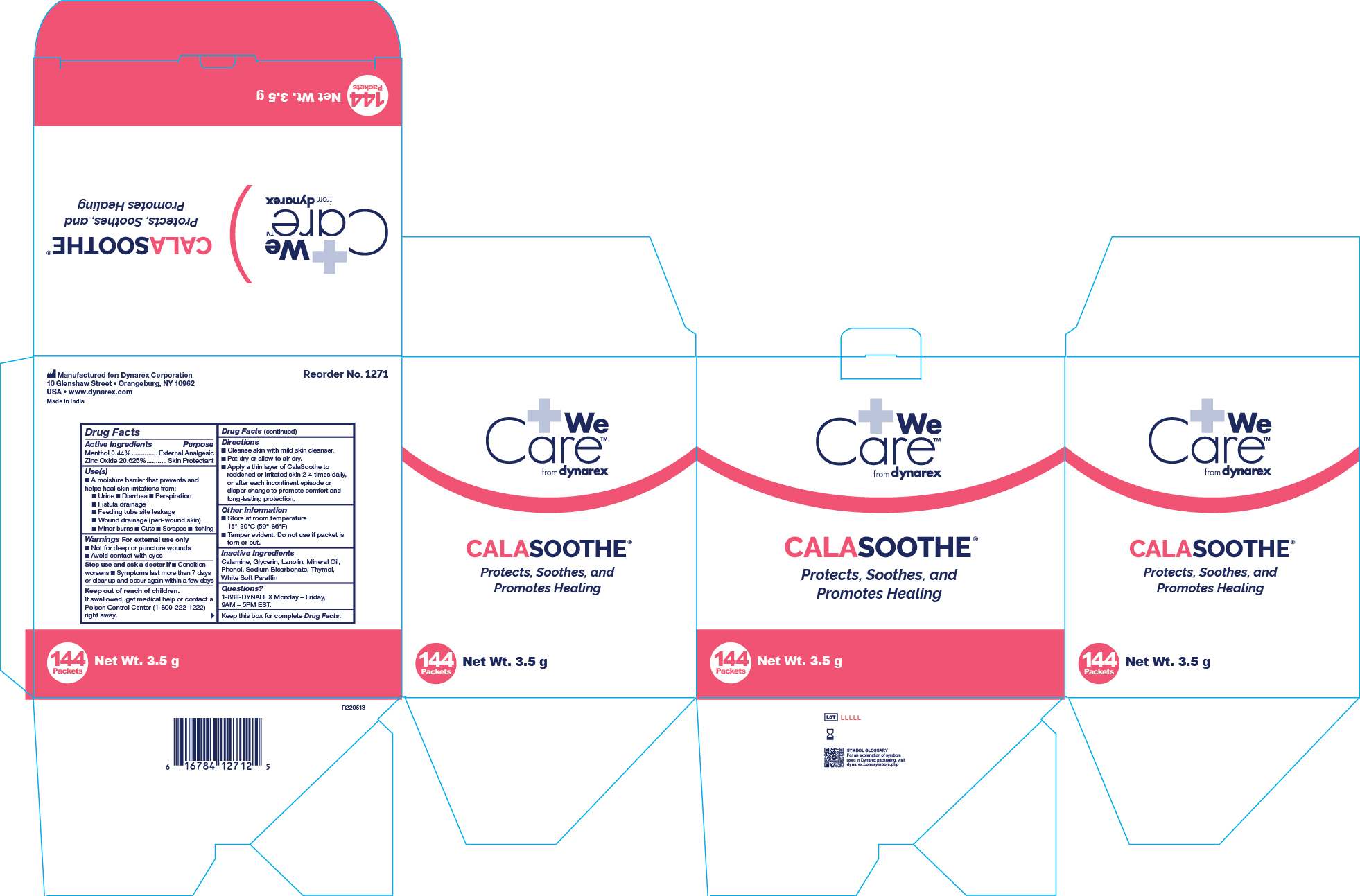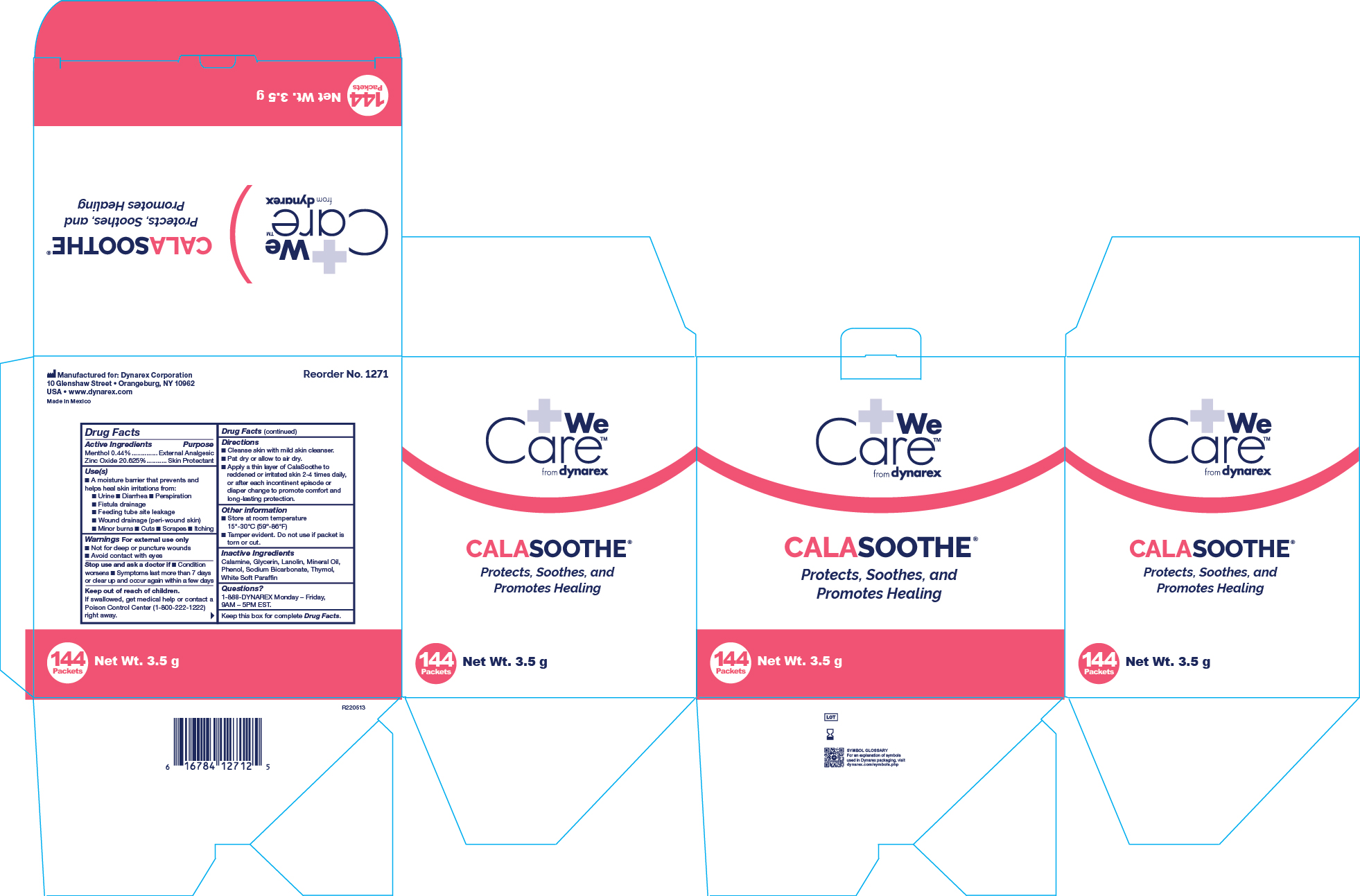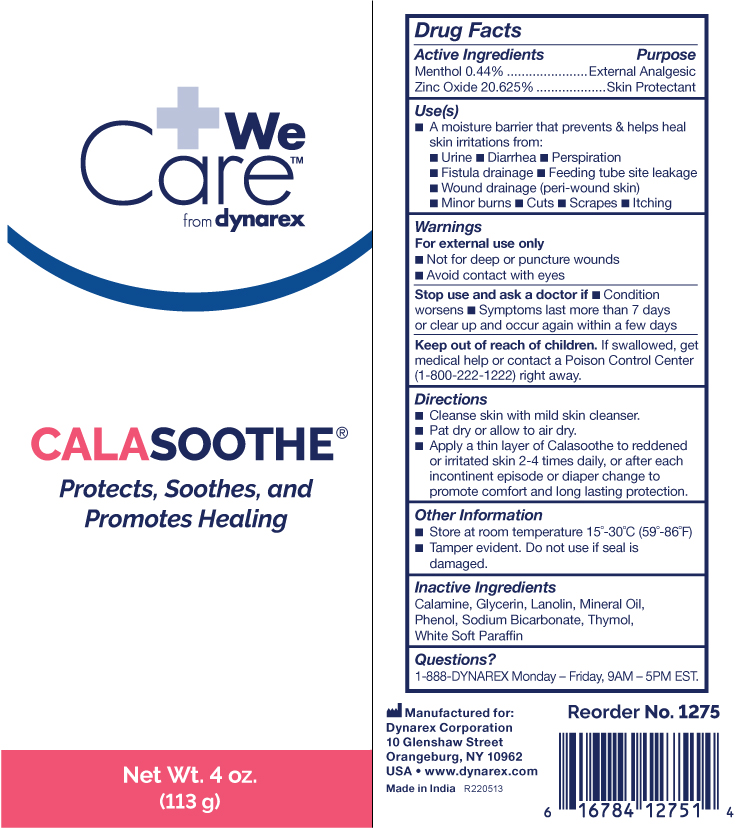 DRUG LABEL: Menthol and Zinc Oxide
NDC: 67777-234 | Form: OINTMENT
Manufacturer: Dynarex Corporation
Category: otc | Type: HUMAN OTC DRUG LABEL
Date: 20241120

ACTIVE INGREDIENTS: MENTHOL 0.44 g/100 g; ZINC OXIDE 21 g/100 g
INACTIVE INGREDIENTS: FERRIC OXIDE RED; WHITE PETROLATUM; GLYCERIN; PHENOL; LANOLIN; MINERAL OIL; SODIUM BICARBONATE; THYMOL

1271 Calasoothe Ointment NDC 67777-234-01
1275 Calasoothe Ointment NDC 67777-234-03

Active Ingredient

Menthol 0.44%

Zinc Oxide 20.625%

Purpose

External Analgesic

Skin Protectant

Uses

• A moisture barrier that prevents and helps heal skin irritations from:

• Urine • Diarrhea • Perspiration • Fistula drainage • Feeding tube site leakage • Wound drainage (peri-wound skin) • Minor burns

• Cuts • Scrapes • Itching

Warnings

For external use only

When using this product

• Avoid contact with eyes

Do not use section

• On deep or puncture wounds

Stop use and ask a doctor if

• Condition worsens • Symptoms last more than 7 days or clear up and occur again within a few days

Keep Out Of Reach Of Children

If swallowed, get medical help or contact a Poison Control Center (1-800-222-1222) right away.

Directions

• Cleanse skin with mild skin cleanser.

• Pat dry or allow to air dry.

• Apply a thin layer of Calasoothe to reddened or irritated skin 2-4 times daily, or after each incontinent episode or diaper change to promote comfort and long lasting protection.

Other Information

• Store at room temperature 15º-30º C (59º-86º F)

• Tamper evident. Do not use if packet is torn or cut. Do not use if seal is damaged.

Inactive Ingredients

Calamine, Glycerine, Lanolin, Mineral Oil, Phenol, Sodium Bicarbonate, Thymol, White Soft Paraffin

Questions?

1-888-DYNAREX Monday - Friday, 9AM - 5PM EST

Label

Calasoothe 4 oz. tube

Label

1271 Calasoothe